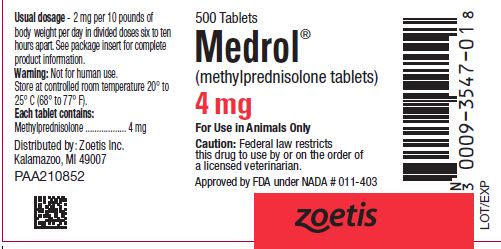 DRUG LABEL: Medrol
NDC: 54771-3547 | Form: TABLET
Manufacturer: Zoetis Inc.
Category: animal | Type: PRESCRIPTION ANIMAL DRUG LABEL
Date: 20230911

ACTIVE INGREDIENTS: METHYLPREDNISOLONE 4 mg/1 1

Medrol®

SAFE HANDLING WARNING

Medrol®
(methylprednisolone tablets)

For Oral Use in Dogs and Cats

Caution: Federal law restricts this drug to use by or on the order of a licensed veterinarian.

DESCRIPTION

Methylprednisolone, a potent anti-inflammatory steroid synthesized and developed in the Research Laboratories of The Upjohn Company is the 6-methyl derivative of prednisolone. It has a greater anti-inflammatory potency than prednisolone and even less tendency than prednisolone to induce sodium and water retention. Its advantage over the older corticoids lies in its ability to achieve equal anti-inflammatory effect with lower dose, while at the same time enhancing the split between anti-inflammatory and mineralocorticoid activities.

INDICATIONS

The indications for MEDROL Tablets are the same as those for other anti-inflammatory steroids and comprise the various collagen, dermal, allergic, ocular, otic, and musculoskeletal conditions known to be responsive to the anti-inflammatory corticosteroids. Representative of the conditions in which the use of steroid therapy and the benefits to be derived therefrom have had repeated confirmation in the veterinary literature are: (1) dermal conditions, such as non-specific eczema, summer dermatitis, and burns; (2) allergic manifestations, such as acute urticaria, allergic dermatitis, drug and serum reactions, bronchial asthma, and pollen sensitivities; (3) ocular conditions, such as iritis, iridocyclitis, secondary glaucoma, uveitis, and chorioretinitis; (4) otic conditions, such as otitis externa; (5) musculoskeletal conditions, such as myositis, rheumatoid arthritis, osteoarthritis, and bursitis; (6) various chronic or recurrent diseases of unknown etiology such as ulcerative colitis and nephrosis.

In acute adrenal insufficiency, MEDROL may be effective because of its ability to correct the defect in carbohydrate metabolism and relieve the impaired diuretic response to water characteristic of primary or secondary adrenal insufficiency. However, because this agent lacks significant mineralocorticoid activity, the parent hormones, SOLU-CORTEF® containing hydrocortisone sodium succinate, CORTEF® containing hydrocortisone, or cortisone should be used when salt retention is indicated.

CONTRAINDICATIONS

MEDROL Tablets like prednisolone, are contraindicated in animals with arrested tuberculosis, peptic ulcer, acute psychoses, and Cushingoid syndrome. The presence of diabetes, osteoporosis, chronic psychotic reactions, predisposition to thrombophlebitis, hypertension, congestive heart failure, renal insufficiency, and active tuberculosis necessitates carefully controlled use. Some of the above conditions occur only rarely in dogs and cats but should be kept in mind.

WARNINGS

Not for human use.

Clinical and experimental data have demonstrated that corticosteroids administered orally or parenterally to animals may induce the first stage of parturition when administered during the last trimester of pregnancy and may precipitate premature parturition followed by dystocia, fetal death, retained placenta, and metritis.

Additionally, corticosteroids administered to dogs, rabbits and rodents during pregnancy have resulted in cleft palate in offspring. Corticosteroids administered to dogs during pregnancy have also resulted in other congenital anomalies including deformed forelegs, phocomelia, and anasarca.

PRECAUTIONS

Because of its inhibitory effect on fibroplasia, methylprednisolone may mask the signs of infection and enhance dissemination of the infecting organism. Hence, all animal patients receiving methylprednisolone should be watched for evidence of intercurrent infection. Should infection occur, it must be brought under control by use of appropriate antibacterial measures, or administration of methylprednisolone should be discontinued.

MEDROL Tablets, like prednisolone and other adrenocortical steroids is a potent therapeutic agent influencing the biochemical behavior of most, if not all, tissues of the body. Because this anti-inflammatory steroid manifests little sodium-retaining activity, the usual early sign of cortisone or hydrocortisone overdosage (ie, increase in body weight due to fluid retention) is not a reliable index of overdosage. Hence, recommended dose levels should not be exceeded, and all animal patients receiving MEDROL should be under close medical supervision. All precautions pertinent to the use of prednisolone apply to methylprednisolone. Moreover, the veterinarian should endeavor to keep informed of current studies with MEDROL as they are reported in the veterinary literature.

ADVERSE REACTIONS

With therapeutically equivalent doses, the likelihood of occurrence of troublesome side effects is less with methylprednisolone than with prednisolone; moreover, side effects actually have been conspicuously absent during clinical trials with MEDROL Tablets in dogs and cats. However, methylprednisolone is similar to prednisolone in regard to kinds of side effects and metabolic alterations to be anticipated when treatment is intensive or prolonged. In animal patients with diabetes mellitus, use of methylprednisolone may be associated with an increase in the insulin requirement. Negative nitrogen balance may occur, particularly in animals that require protracted maintenance therapy; measures to counteract persistent nitrogen loss include a high protein intake and the administration when indicated, of a suitable anabolic agent. Excessive loss of potassium, like excessive retention of sodium, is not likely to be induced by effective maintenance doses of MEDROL. However, these effects should be kept in mind and the usual regulatory measures employed as indicated. Ecchymotic manifestations, while not noted during the clinical evaluation in dogs and cats, may occur. If such reactions do occur and are serious, reduction in dosage or discontinuance of methylprednisolone therapy may be indicated. Concurrent use of daily oral supplements of ascorbic acid may be of value in helping to control ecchymotic tendencies.

Since methylprednisolone, like prednisolone, suppresses endogenous adrenocortical activity, it is highly important that the animal patient receiving MEDROL be under careful observation, not only during the course of treatment but for some time after treatment is terminated. Adequate adrenocortical supportive therapy with cortisone or hydrocortisone, and including ACTH, must be employed promptly if the animal is subjected to any unusual stress such as surgery, trauma, or severe infection.

DOSAGE AND ADMINISTRATION

The keystone of satisfactory therapeutic management with MEDROL Tablets, as with its steroid predecessors, is individualization of dosage in reference to the severity of the disease, the anticipated duration of steroid therapy, and the animal patient's threshold or tolerance for steroid excess.

The prime objective of steroid therapy should be to achieve a satisfactory degree of control with a minimum effective daily dose.

The dosage recommendations are suggested average total daily doses and are intended as guides. As with other orally administered corticosteroids, the total daily dose of MEDROL should be given in equally divided doses. The initial suppressive dose level is continued until a satisfactory clinical response is obtained, a period usually of 2 to 7 days in the case of musculoskeletal diseases, allergic conditions affecting the skin or respiratory tract, and ocular inflammatory diseases. If a satisfactory response is not obtained in 7 days, reevaluation of the case to confirm the original diagnosis should be made. As soon as a satisfactory clinical response is obtained, the daily dose should be reduced gradually, either to termination of treatment in the case of acute conditions (eg, seasonal asthma, dermatitis, acute ocular inflammations) or to the minimal effective maintenance dose level in the case of chronic conditions (eg, rheumatoid arthritis). In chronic conditions, and in rheumatoid arthritis especially, it is important that the reduction in dosage from initial to maintenance dose levels be accomplished slowly. The maintenance dose level should be adjusted from time to time as required by fluctuation in the activity of the disease and the animal's general status. Accumulated experience has shown that the long-term benefits to be gained from continued steroid maintenance are probably greater the lower the maintenance dose level. In rheumatoid arthritis in particular, maintenance steroid therapy should be at the lowest possible level.

Important: In the therapeutic management of animal patients with chronic diseases such as rheumatoid arthritis, methylprednisolone should be regarded as a highly valuable adjunct, to be used in conjunction with but not as replacement for standard therapeutic measures.

Average total daily oral doses for dogs and cats:

5 to 15 lb body wt | 2 mg
15 to 40 lb body wt | 2 to 4 mg
40 to 80 lb body wt | 4 to 8 mg

The total daily dose should be given in divided doses, 6 to 10 hours apart.

HOW SUPPLIED

Veterinary MEDROL Tablets are compressed cross-scored tablets available in bottles of 500. Each 4 mg tablet contains 4 mg methylprednisolone.

STORAGE AND HANDLING

Store at controlled room temperature 20° to 25° C (68° to 77° F).

Approved by FDA under NADA # 011-403
zoetis
Distributed by:
Zoetis Inc.
Kalamazoo, MI 49007
Revised: June 2023
PAA210851

PRINCIPAL DISPLAY PANEL - 4 mg Tablet Bottle Label

PAA210852